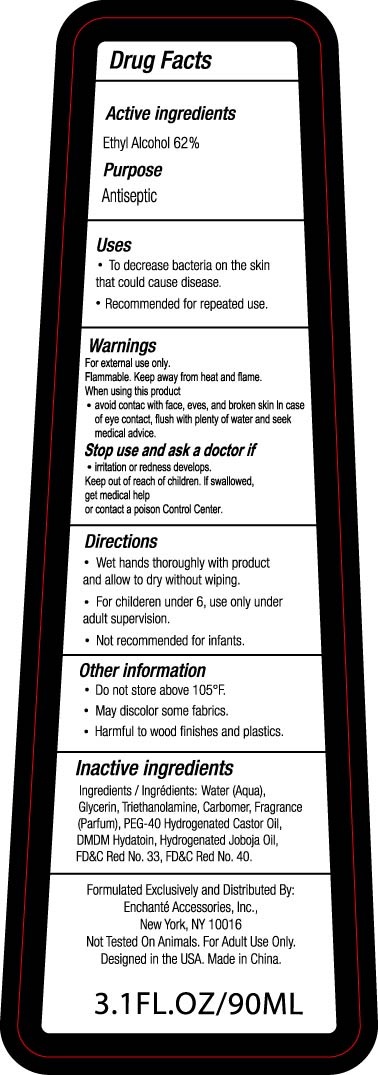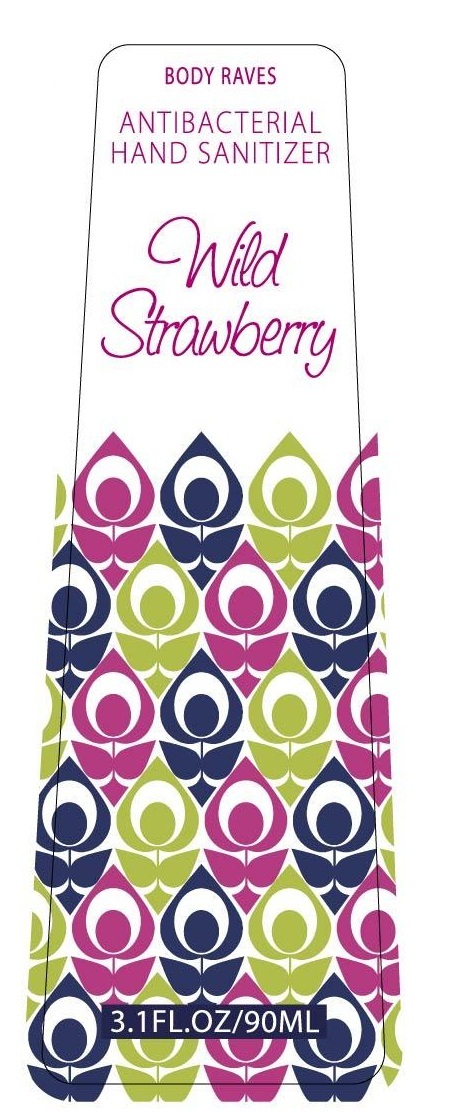 DRUG LABEL: Body Raves Antibacterial Hand Sanitizer - Wild Strawberry
NDC: 50563-154 | Form: LIQUID
Manufacturer: Enchante Accessories
Category: otc | Type: HUMAN OTC DRUG LABEL
Date: 20100623

ACTIVE INGREDIENTS: ALCOHOL 62 mL/100 mL
INACTIVE INGREDIENTS: WATER; GLYCERIN; TROLAMINE; POLYOXYL 40 HYDROGENATED CASTOR OIL; DMDM HYDANTOIN; JOJOBA OIL

BODY RAVES ANTIBACTERIAL HAND SANITIZER WILD STRAWBERRY

DRUG FACTS

Active Ingredients Purpose

Ethyl Alcohol 62% Antiseptic

Uses

To decrease bacteria on the skin that could cause disease

Recommended for repeated use.

Warnings:

For external use only

Flammable

Keep away from heat and flame.

When using this product

Avoid contact with face, eyes and broken skin.

In case of eye contact, flush with plenty of water and seek medical advice.

PEEL UP TO SEE MORE INFORMATON

Stop use and ask a doctor if:

irritation or redness develops.

Keep out of reach of children.

If swallowed get medical help or contact a poison control center.

Directions

Wet hands thoroughly with product and allow to dry without wiping

For children under 6, use only under adult supervision

Not recommended for infants.

Other information

Do not store above 105 degrees F

May discolor some fabrics

Harmful to wood finishes and plastics.

Inactive ingredients

Ingredients/Ingredients: Alcohol, Water (aqua), Glycerin

Triethanolamine, Carbomer, PEG-40 Hydrogenated Castor Oil, DMDM Hydantoin, Hydrogenated Jojoba Oil, FD and C Red No 33, FD and C Red No. 40

Formulated Exclusively and Distributed by:

Enchante Accessories, Inc.,

New York, NY 10016

Not tested on animals. For adult use only

Designed in the USA. Made in China

3.1 Fl oz/90 ml

PACKAGE LABEL

BODY RAVES
ANTIBACTERIAL
HAND SANITIZER
LAVENDER VANILLA
3.1 FL OZ / 90 ML